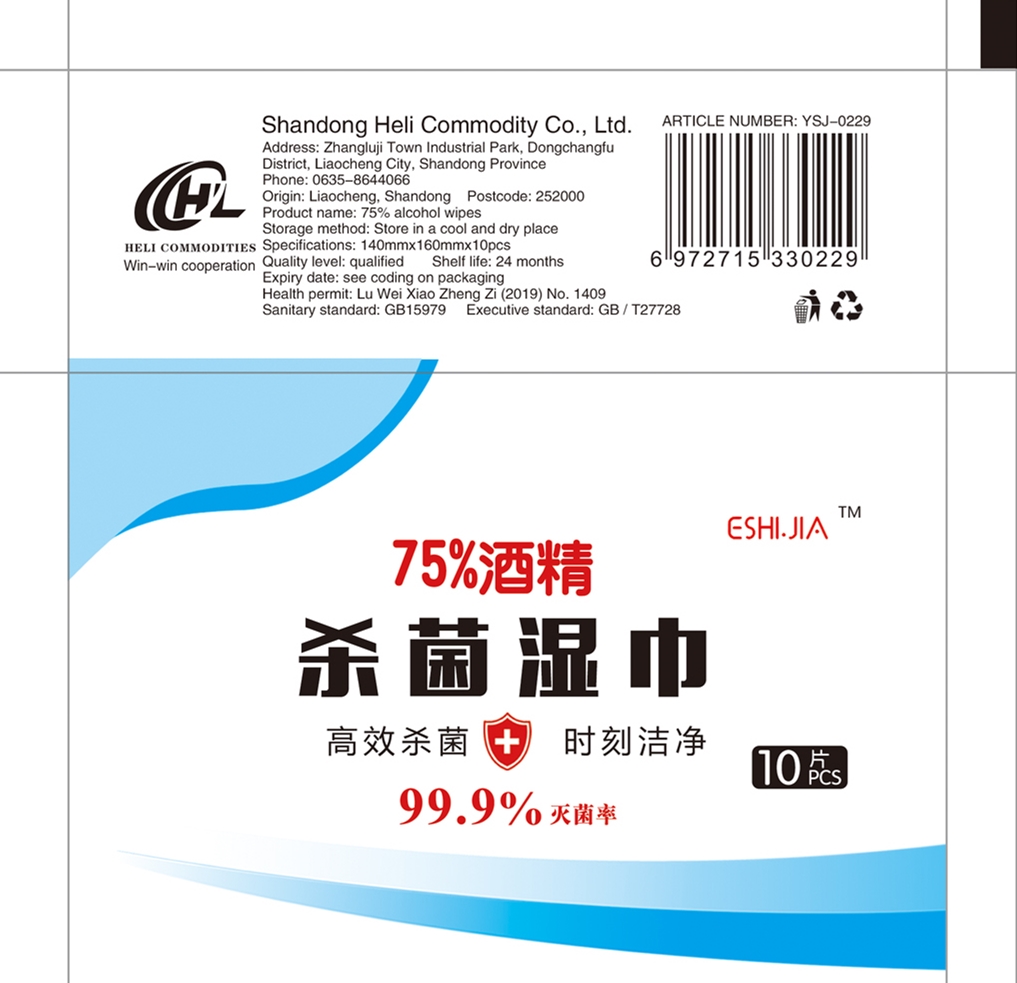 DRUG LABEL: 75% Alcohol Wipes
NDC: 55676-001 | Form: CLOTH
Manufacturer: SHANDONG HELI DAILY NECESSITIES CO.,LTD
Category: otc | Type: HUMAN OTC DRUG LABEL
Date: 20200907

ACTIVE INGREDIENTS: ALCOHOL 15 mL/10 1
INACTIVE INGREDIENTS: WATER

DOSAGE AND ADMINISTRATION

Store in a cool and dry place

INACTIVE INGREDIENT

water

INDICATIONS AND USAGE

Open the package and take out the paper towel to wipe

ACTIVE INGREDIENT

alcohol

keep out of reach of children

PURPOSE

Disinfection
Sterilization
No Rinseing

WARNINGS

For external use only- Highly Flammable,Keep away from fire or flame.